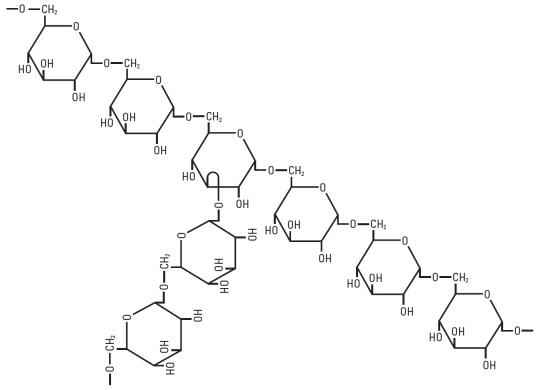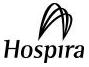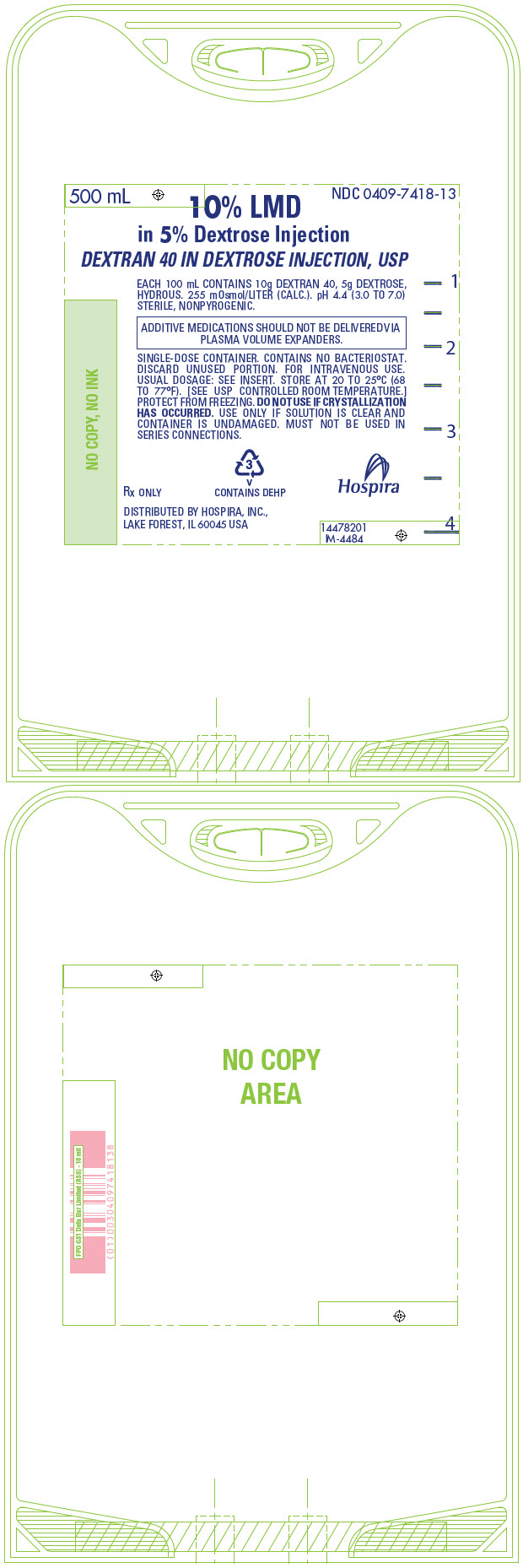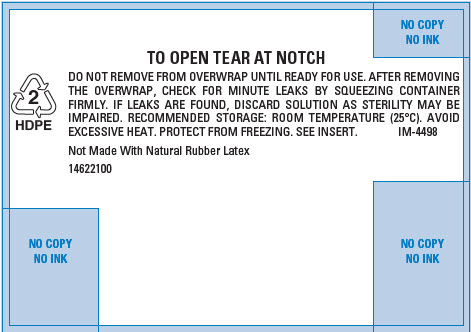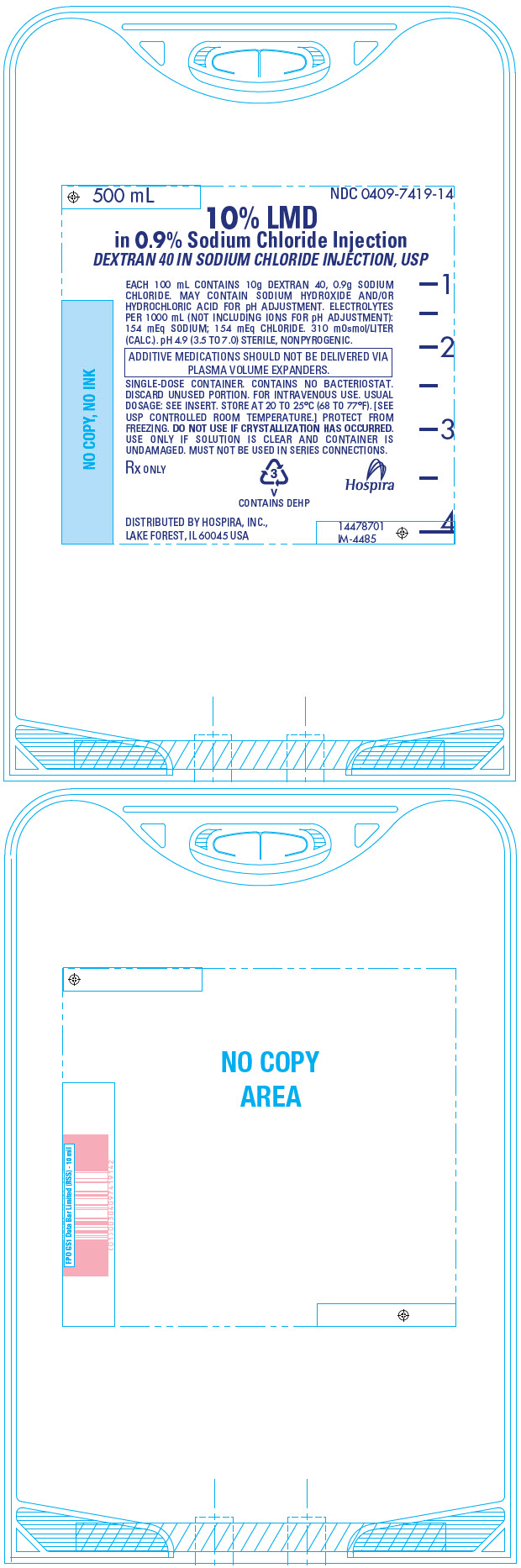 DRUG LABEL: LMD in Dextrose
NDC: 0409-7418 | Form: INJECTION, SOLUTION
Manufacturer: Hospira, Inc.
Category: prescription | Type: HUMAN PRESCRIPTION DRUG LABEL
Date: 20250702

ACTIVE INGREDIENTS: DEXTRAN 40 10 g/100 mL
INACTIVE INGREDIENTS: WATER; DEXTROSE MONOHYDRATE

10% LMD in 5% Dextrose Injection Rx only
(Dextran 40 in Dextrose Injection, USP)

10% LMD in 0.9% Sodium Chloride Injection
(Dextran 40 in Sodium Chloride Injection, USP)

Low Molecular Weight Dextran for Intravenous Administration

Flexible Plastic Container

DESCRIPTION

LMD (dextran 40) is a sterile, nonpyrogenic preparation of low molecular weight dextran (average mol. wt. 40,000) in 5% Dextrose Injection or 0.9% Sodium Chloride Injection. It is administered by intravenous infusion.

Also described as low viscous or low viscosity dextran, dextran 40 is prepared by acid hydrolysis and differential fractionation of a crude macromolecular polysaccharide produced from the fermentation of sucrose by the bacterium, Leuconostoc mesenteroides (strain B-512). The crude material is composed of linked glucose units. In the fraction represented by dextran 40, 80% of the molecules have a molecular weight ranging from 10,000 to 90,000 (average approximately 40,000) when measured by a light scattering method. More than 90% of the linkages are of the 1,6 alpha glucosidic, straight chain type.

Each 100 mL of 10% LMD (dextran 40) in 5% Dextrose Injection contains 10 g dextran 40 and 5 g dextrose hydrous in water for injection. Total osmolar concentration is 255 mOsmol/liter (calc.); pH is 4.4 (3.0 to 7.0).

Each 100 mL of 10% LMD (dextran 40) in 0.9% Sodium Chloride Injection contains 10 g dextran 40 and 0.9 g sodium chloride in water for injection. Total osmolar concentration is 310 mOsmol/liter (calc.); pH is 4.9 (3.5 to 7.0) (may contain sodium hydroxide and/or hydrochloric acid for pH adjustment). Electrolyte concentration per liter: Na^+ 154 mEq; Cl^- 154 mEq (not including ions for pH adjustment).

The solutions contain no bacteriostat, antimicrobial agent or added buffers (except for pH adjustment) and are intended only for single-dose injection. When smaller doses are required the unused portion should be discarded.

10% LMD (dextran 40) is an artificial colloid pharmacologically classified as a plasma volume expander; 5% Dextrose Injection is a fluid and nutrient replenisher; 0.9% Sodium Chloride Injection is a fluid and electrolyte replenisher.

Dextran 40 is a linear glucose polymer (polysaccharide) chemically designated (C6 H10 O5)n.

The structural formula for dextran (repeating unit) is:

Dextrose, USP is chemically designated D-glucose monohydrate (C6 H12 O6 • H2O), a hexose sugar freely soluble in water.

Sodium Chloride, USP is chemically designated NaCl, a white crystalline powder freely soluble in water.

Water for Injection, USP is chemically designated H2O.

The flexible plastic container is fabricated from a specially formulated polyvinylchloride. Water can permeate from inside the container into the overwrap but not in amounts sufficient to affect the solution significantly. Solutions inside the plastic container also can leach out certain of the chemical components of the plastic in very small amounts before the expiration period is attained. However, safety of the plastic has been confirmed by tests in animals according to USP biological standards for plastic containers.

CLINICAL PHARMACOLOGY

The fundamental action of LMD (dextran 40) is the enhancement of blood flow, particularly in the microcirculation. This enhancement is due to:

1. Its primary effect of volume expansion with resultant hemodilution;
2. Maintenance of the electronegativity of red blood cells;
3. Coating of red blood cells and platelets;
4. Increase in the suspension stability of blood;
5. Decrease in the viscosity of blood.

It should be emphasized that the above effects are not exerted separately, but conjointly they result in the enhancement of blood flow.

LMD, used in the treatment of shock, produces significant increases in blood volume, central venous pressure, cardiac output, stroke volume, blood pressure and urinary output. It reduces blood viscosity, peripheral resistance and improves peripheral blood flow with the release of sequestered blood cells, thereby increasing venous return to the heart.

When used as part of the pump prime for extracorporeal procedures, LMD, as compared to whole blood, albumin 5%, or whole blood plus 5% dextrose and water, leads to less destruction of red blood cells and platelets, reduces intravascular hemagglutination and maintains erythrocyte electronegativity.

The infusion of LMD (dextran 40) during and after surgical trauma reduces the incidence of deep venous thrombosis (DVT) and pulmonary embolism (PE) in patients subject to surgical procedures with a high incidence of thromboembolic complication. Unlike antithrombogenic agents of the anticoagulant type, LMD does not achieve its effect so much by blocking fibrinogen-fibrin conversion but acts by simultaneously inhibiting other mechanisms essential to thrombus formation such as vascular stasis and platelet adhesiveness and by altering the structure and thereby the lysability of fibrin clots.

Histopathological studies have shown that the development of a mural platelet thrombus is the first stage of thrombus formation not only in the arterial, but also in the venous system. A number of studies have further shown that many patients who develop thromboembolic complications show an abnormally high platelet adhesiveness. Infusion of LMD has been shown to reduce platelet adhesiveness as measured by various in vitro tests on blood samples obtained from humans and to inhibit the growth of a mural platelet thrombus at the site of experimental (laser beam) injury in the rabbit's ear chamber.

Studies have shown an increase in the lysability of thrombi formed in the presence of dextran. A consistent and characteristic alteration in fibrin structure has been observed when fibrin is formed in the presence of dextran, and further experiments demonstrated such fibrin to be more susceptible to plasmin digestion. Other studies have shown that dextran infused into patients during surgery increases the lysability of ex vivo thrombi. Controlled clinical trials have shown that thrombi in patients treated with dextran have a more pronounced tendency to undergo lysis as determined by phlebography.

LMD is evenly distributed in the vascular system. Its distribution according to molecular weight shifts toward higher molecular weights as the smaller molecules are excreted by the kidney. In normovolemic subjects, approximately 50% is excreted within 3 hours, 60% is excreted within 6 hours and about 75% within 24 hours. Reabsorption of dextran by the renal tubules is negligible. The unexcreted molecules of dextran diffuse into the extravascular compartment and are temporarily taken up by the reticuloendothelial system. Some of these molecules are returned to the intravascular compartment via the lymphatics. Dextran is slowly degraded by the enzyme dextranase to glucose.

Solutions containing carbohydrate in the form of dextrose restore blood glucose levels and provide calories. Carbohydrate in the form of dextrose may aid in minimizing liver glycogen depletion and exerts a protein sparing action. Dextrose injected parenterally undergoes oxidation to carbon dioxide and water.

Sodium chloride in water dissociates to provide sodium (Na^+) and chloride (Cl^-) ions. Sodium (Na^+) is the principal cation of the extracellular fluid and plays a large part in the therapy of fluid and electrolyte disturbances. Chloride (Cl^-) has an integral role in buffering action when oxygen and carbon dioxide exchange occurs in red blood cells. The distribution and excretion of sodium (Na^+) and chloride (Cl^-) are largely under the control of the kidney, which maintains a balance between intake and output.

Water is an essential constituent of all body tissues and accounts for approximately 70% of total body weight. Average normal adult daily requirement ranges from two to three liters (1.0 to 1.5 liters each for insensible water loss by perspiration and urine production).

Water balance is maintained by various regulatory mechanisms. Water distribution depends primarily on the concentration of electrolytes in the body compartments and sodium (Na^+) plays a major role in maintaining physiologic equilibrium.

INDICATIONS AND USAGE

LMD (dextran 40) is indicated for use in the adjunctive treatment of shock or impending shock due to hemorrhage, burns, surgery or other trauma. It is not indicated as a replacement for whole blood or blood components if they are available. It should not replace other forms of therapy known to be of value in the treatment of shock.

LMD is also indicated for use as a priming fluid, either as a sole prime or as an additive, in pump oxygenators during extracorporeal circulation.

LMD is also indicated for use in prophylaxis of venous thrombosis and pulmonary embolism in patients undergoing procedures known to be associated with a high incidence of thromboembolic complications, such as hip surgery.

CONTRAINDICATIONS

LMD (dextran 40) is contraindicated in patients with known hypersensitivity to dextran, in those with marked hemostatic defects of all types (thrombocytopenia, hypofibrinogenemia, etc.) including those caused by drugs (heparin, warfarin, etc.), marked cardiac decompensation and in renal disease with severe oliguria or anuria.

WARNINGS

Although infrequent, severe and fatal anaphylactoid reactions consisting of marked hypotension or cardiac and respiratory arrest have been reported, most of these reactions have occurred in patients not previously exposed to intravenous dextran and early in the infusion period. It is strongly recommended, therefore, that patients not previously exposed to dextran be observed closely during the first minutes of the infusion period.

Anaphylactoid Reactions

There have been rare reports of serious and life-threatening dextran-induced anaphylactoid reactions (DIAR) associated with Dextran 40 and Dextran 70 administration. To reduce the likelihood of DIAR, 20 mL dextran 1 should be administered prior to infusion of Dextran 40 or Dextran 70 consistent with the dextran 1 package insert.^1-5 See DOSAGE AND ADMINISTRATION. Investigators have reported a 35-fold decrease (from 1:2000 to 1:70,000) in the incidence of DIAR following prophylactic use of dextran 1.^6 However, serious and life-threatening reactions may still occur following initiation of an infusion of any clinical dextran (see ADVERSE REACTIONS).

Because of the seriousness of anaphylactoid reactions, it is recommended that the infusion of intravenous dextran be stopped at the first sign of an allergic reaction provided that other means of sustaining the circulation are available. Resuscitative measures should be readily available for emergency administration in the event such a reaction occurs. In circulatory collapse due to anaphylaxis, rapid volume substitutions with an agent other than dextran should be instituted.

Because LMD (dextran 40) is a hypertonic colloid solution, it attracts water from the extravascular space. This shift of fluid should be considered if the drug is used for poorly hydrated patients where additional fluid therapy will be needed. If LMD is given in excess, vascular overload could occur. The latter possibility can be avoided with careful clinical monitoring preferably by central venous pressure.

Renal excretion of LMD causes elevations of the specific gravity of the urine. In the presence of adequate urine flow only minor elevation will occur, whereas in patients with reduced urine output, urine viscosity and specific gravity can be increased markedly. Since urine osmolarity is only slightly increased by the presence of dextran molecules, it is recommended that, when desired, a patient's state of hydration be assessed by determination of urine or serum osmolarity. If signs of dehydration are present, additional fluid should be administered. An osmotic diuretic such as mannitol also can be used to maintain an adequate urine flow.

Although numerous studies attest to the "nephrotonic" effect of LMD, renal failure has been reported to occur after the use of LMD.

Evidence of tubular vacuolization (osmotic nephrosis) has been found following LMD administration in animals and man. While this appears to be reversible experimentally in animals and to be a consequence of high urine concentration of the drug, its exact clinical significance is presently unknown.

Occasional abnormal renal and hepatic function values have been reported following administration of LMD. However, the specific effect of LMD on renal and hepatic function could not be determined because most of the patients also had undergone surgery or cardiac catheterization. A comparative study of dextran 40 and 5% dextrose in water as pump-priming fluids in open-heart surgery has shown similar elevations of serum glutamic oxaloacetic transaminase (SGOT), aspartate aminotransferase and serum glutamic pyruvic transaminase (SGPT), alanine aminotransferase values in both groups.

Caution should be employed when LMD is administered to patients with active hemorrhage as the resulting increase in perfusion pressure and improved microcirculatory flow may result in additional blood loss.

Administering infusions of LMD that exceed the recommended dose should be avoided, since a dose-related increase in the incidence of wound hematoma, wound seroma, wound bleeding, distant bleeding (hematuria and melena) and pulmonary edema has been observed. Recommended doses should never be exceeded in patients with advanced renal disease, since excessive doses may precipitate renal failure.

Dextran may interfere to some extent with platelet function and should be used with caution in cases with thrombocytopenia. Transient prolongation of bleeding time and/or slightly increased bleeding tendency may occur with the administration of doses greater than 1,000 mL. Care should be taken to prevent a depression of hematocrit below 30% by volume. When large volumes of dextran are administered, plasma protein levels will be decreased.

Solutions containing sodium ions should be used with great care, if at all, in patients with congestive heart failure, severe renal insufficiency and in clinical states in which there exists edema with sodium retention.

The intravenous administration of this solution can cause fluid and/or solute overloading resulting in dilution of serum electrolyte concentrations, overhydration, congested states or pulmonary edema. The risk of dilutional states is inversely proportional to the electrolyte concentrations of administered parenteral solutions.

The risk of solute overload causing congested states with peripheral and pulmonary edema is directly proportional to the electrolyte concentrations of such solutions.

In patients with diminished renal function, administration of solutions containing sodium ions may result in sodium retention.

PRECAUTIONS

The possibility of circulatory overload should be kept in mind. Special care should be exercised in patients with impaired renal clearance of dextran. When the risk of pulmonary edema and/or congestive heart failure may be increased, dextran should be used with caution.

In patients with normal hemostasis, dosage of LMD (dextran 40) approximating 15 mL/kg of body weight may prolong bleeding time and depress platelet function. Dosages in this range also markedly decrease factor VIII, and decrease factors V and IX to a greater degree than would be expected to occur from hemodilution alone. Since these changes tend to be more pronounced following trauma or major surgery, patients should be observed for early signs of bleeding complications.

Since increased rouleaux formation may occur in the presence of dextran, it is recommended that blood samples be drawn for typing and cross-matching prior to the infusion of dextran and reserved for subsequent use if necessary. If blood is drawn after infusion of dextran, the saline agglutination and indirect antiglobulin methods may be used for typing and cross-matching. Difficulty may be encountered when proteolytic enzyme techniques are used to match blood.

Consideration should be given to withdrawal of blood for chemical laboratory tests prior to initiating therapy with dextran because of the following:

1. Blood sugar determinations that employ high concentrations of acid may result in hydrolysis of dextran, yielding falsely elevated glucose assay results. This has been observed both with sulfuric acid and with acetic acid.
2. In other laboratory tests, the presence of dextran in the blood may result in the development of turbidity, which can interfere with the assay. This has been observed in bilirubin assays in which alcohol is employed and in total protein assays employing biuret reagent.

Solutions containing dextrose should be used with caution in patients with known subclinical or overt diabetes mellitus.

Caution must be exercised in the administration of parenteral fluids, especially those containing sodium ions, to patients receiving corticosteroids or corticotropin.

Do not administer unless solution is clear and container is undamaged. Discard unused portion.

Drug Interactions. Additive medications should not be delivered via plasma volume expanders.

Pregnancy. Animal reproduction studies have not been conducted with dextran 40 in dextrose or sodium chloride. It is also not known whether dextran 40 in dextrose or sodium chloride can cause fetal harm when administered to a pregnant woman or can affect reproduction capacity. 10% LMD (dextran 40) in dextrose or sodium chloride should be given to a pregnant woman only if clearly needed.

Nursing Mothers. It is not known whether this drug is excreted in human milk. Because many drugs are excreted in human milk, caution should be exercised when 10% LMD (dextran 40) in dextrose or sodium chloride is administered to a nursing woman.

Pediatric Use. The safety and effectiveness of dextran 40 have not been established in neonates. Its limited use in neonates has been inadequate to fully define proper dosage and limitations for use.

ADVERSE REACTIONS

Antigenicity of dextrans is directly related to their degree of branching. Since LMD (dextran 40) has a low degree of branching, it is relatively free of antigenic effect. However, a few individuals have experienced mild urticarial reactions. More severe reactions, consisting of severe anaphylactoid reaction, generalized urticaria, tightness of the chest, wheezing, hypotension, nausea and vomiting may occur in rare instances. Symptoms and signs of adverse systemic reaction may be relieved by parenteral administration of antihistamines, ephedrine or epinephrine, while other means of shock therapy are instituted. The route of administration and dosages of the therapeutic agent selected will depend upon the severity and rapidity of progression of the reaction.

Reactions which may occur because of the solution or the technique of administration include febrile response, infection at the site of injection, venous thrombosis or phlebitis extending from the site of injection, extravasation and hypervolemia.

If an adverse reaction does occur, discontinue the infusion, evaluate the patient, institute appropriate therapeutic countermeasures, and save the remainder of the fluid for examination if deemed necessary (see WARNINGS for treatment of anaphylactic shock).

Post Marketing

Severe reactions have been observed with Dextran 40 and Dextran 70. Reported reactions include: generalized urticaria, nausea and vomiting, wheezing, hypotension, shock and cardiac arrest (dextran-induced anaphylactoid reactions, DIAR). FDA has received 94 reports of severe DIAR since 1964. Because these reactions are reported voluntarily and the treated population is of indeterminate size, the frequency of reactions cannot be estimated reliably.

DOSAGE AND ADMINISTRATION

LMD (dextran 40) is administered by I.V. infusion only.

Dextran 1 should be administered prior to administration of clinical dextran solutions.

1. In shock, it is suggested that total dosage not exceed 20 mL/kg for adults and adolescents, during the first 24 hours. The first 10 mL/kg may be infused as rapidly as necessary to effect improvement. It is strongly recommended that central venous pressure be monitored frequently during the initial infusion of the drug. Should therapy continue beyond 24 hours, subsequent dosage should not exceed 10 mL/kg per day and therapy should not continue beyond five days.
2. In extracorporeal perfusion, the dosage of LMD used will vary with the volume of the pump oxygenator. LMD can serve as a sole primer or as an additive to other priming fluids. For adults and adolescents, generally 10 to 20 mL of a 10% solution (1 to 2 g) of LMD per kilogram of body weight are added to the perfusion circuit. Usually total dosage should not exceed 2 g/kg of body weight.
3. In prophylaxis of venous thrombosis and thromboembolism, the dosage of LMD for adults and adolescents, should be chosen according to the risk of thromboembolic complications, e.g., type of surgery and duration of immobilization. In general, treatment should be initiated during surgery; 500 to 1,000 mL (approximately 10 mL/kg of body weight) should be administered on the day of operation. Treatment should be continued at a dose of 500 mL daily for an additional two to three days; then, according to the risk of complications, 500 mL may be given every second or third day during the period of risk, for up to two weeks.
4. Infants may be given 5 mL per kg body weight and children 10 mL per kg.

Parenteral drug products should be inspected visually for particulate matter and discoloration prior to administration, whenever solution and container permit. See PRECAUTIONS.

Note: When infusing concentrated LMD, the administration set should include a filter.

Instructions for use

To Open

Tear outer wrap at notch and remove solution container. Some opacity of the plastic due to moisture absorption during the sterilization process may be observed. This is normal and does not affect solution quality or safety. The opacity will diminish gradually.

Preparation for Administration

(Use aseptic technique)

1. Close flow control clamp of administration set.
2. Remove cover from outlet port at bottom of container.
3. Insert piercing pin of administration set into port with a twisting motion until the set is firmly seated. Note: See full directions on administration set carton.
4. Suspend container from hanger.
5. Squeeze and release drip chamber to establish proper fluid level in drip chamber.
6. Open flow control clamp and clear air from set. Close clamp.
7. Attach set to venipuncture device. If device is not indwelling, prime and make venipuncture.
8. Regulate rate of administration with flow control clamp.
WARNING: Do not use flexible container in series connections.

HOW SUPPLIED

10% LMD in 5% Dextrose Injection (Dextran 40 in Dextrose Injection, USP) is supplied as follows:

Unit of Sale | Concentration Dextran 40
NDC 0409-7418-03 Case containing 12 500 mL Single-dose flexible containers | 50 g/500 mL (10 g/100 mL)

10% LMD in 0.9% Sodium Chloride Injection (Dextran 40 in Sodium Chloride Injection, USP) is supplied as follows:

Unit of Sale | Concentration Dextran 40
NDC 0409-7419-03 Case containing 12 500 mL Single-dose flexible containers | 50 g/500 mL (10 g/100 mL)

Do not use if crystallization has occurred.

Store at 20 to 25°C (68 to 77°F). [See USP Controlled Room Temperature.] Protect from freezing.

REFERENCES

1. Richter W. Build-in hapten inhibition of anaphylaxis by the low molecular weight fractions of a B 512 dextran fraction of MW 3400. Int Arch Allergy 1973;45:930
2. Lungstrom K-G, Renck H, Hedin H, et al. Prevention of dextran-induced anaphylactic reactions by hapten inhibition. I. A Scandinavian multicenter study on the effects of 10 mL dextran 1, 15%, administered before Dextran 70 or Dextran 40. Acta Chir Scand 1983;149:341-348
3. Renck H, Ljungstrom K-G, Rosberg B, et al. Prevention of dextran-induced anaphylactic reactions by hapten inhibition. II. A comparison of the effects of 20 mL dextran 1, 15%, administered either admixed to or before Dextran 70 or Dextran 40. Acta Chir Scand 1983;149:349-353
4. Renck H, Ljungstrom K-G, Hedin H, et al. Prevention of dextran-induced anaphylactic reactions by hapten inhibition. III. A Scandinavian multicenter study on the effects of 20 mL dextran 1, 15%, administered before Dextran 70 or Dextran 40. Acta Chir Scand 1983;149:355-360
5. Ljungstrom K-G, Renck H, Strandberg K, et al. Adverse reactions to dextran in Sweden 1970-1979. Acta Chir Scand 1983;149:253-262
6. Hedin H, Ljungstrom K-G. Prevention of dextran anaphylaxis. Ten years experience with hapten dextran. Int Arch Allergy Immunol 1997;113:358-359

Distributed by Hospira, Inc., Lake Forest, IL 60045 USA

LAB-1252-4.0

Revised: 10/2018

PRINCIPAL DISPLAY PANEL - 500 mL Bag - 7418

500 mL

NDC 0409-7418-13

10% LMD
in 5% Dextrose Injection
DEXTRAN 40 IN DEXTROSE INJECTION, USP

EACH 100 mL CONTAINS 10g DEXTRAN 40, 5g DEXTROSE,
HYDROUS. 255 mOsmol/LITER (CALC.). pH 4.4 (3.0 TO 7.0)
STERILE, NONPYROGENIC.

ADDITIVE MEDICATIONS SHOULD NOT BE DELIVERED VIA
PLASMA VOLUME EXPANDERS.

SINGLE-DOSE CONTAINER. CONTAINS NO BACTERIOSTAT.
DISCARD UNUSED PORTION. FOR INTRAVENOUS USE.
USUAL DOSAGE: SEE INSERT. STORE AT 20 TO 25°C (68
TO 77°F). [SEE USP CONTROLLED ROOM TEMPERATURE.]
PROTECT FROM FREEZING. DO NOT USE IF CRYSTALLIZATION
HAS OCCURRED. USE ONLY IF SOLUTION IS CLEAR AND
CONTAINER IS UNDAMAGED. MUST NOT BE USED IN
SERIES CONNECTIONS.

Rx ONLY

3
v
CONTAINS DEHP

Hospira

DISTRIBUTED BY HOSPIRA, INC.,
LAKE FOREST, IL 60045 USA

14478201
IM-4484

PRINCIPAL DISPLAY PANEL - 500 mL Bag Overwrap - 7418

2
HDPE

TO OPEN TEAR AT NOTCH

DO NOT REMOVE FROM OVERWRAP UNTIL READY FOR USE. AFTER REMOVING
THE OVERWRAP, CHECK FOR MINUTE LEAKS BY SQUEEZING CONTAINER
FIRMLY. IF LEAKS ARE FOUND, DISCARD SOLUTION AS STERILITY MAY BE
IMPAIRED. RECOMMENDED STORAGE: ROOM TEMPERATURE (25°C). AVOID
EXCESSIVE HEAT. PROTECT FROM FREEZING. SEE INSERT.
IM-4498

Not Made With Natural Rubber Latex

14622100

PRINCIPAL DISPLAY PANEL - 500 mL Bag - 7419

500 mL

NDC 0409-7419-14

10% LMD
in 0.9% Sodium Chloride Injection
DEXTRAN 40 IN SODIUM CHLORIDE INJECTION, USP

EACH 100 mL CONTAINS 10g DEXTRAN 40, 0.9g SODIUM
CHLORIDE. MAY CONTAIN SODIUM HYDROXIDE AND/OR
HYDROCHLORIC ACID FOR pH ADJUSTMENT. ELECTROLYTES
PER 1000 mL (NOT INCLUDING IONS FOR pH ADJUSTMENT):
154 mEq SODIUM; 154 mEq CHLORIDE. 310 mOsmol/LITER
(CALC.). pH 4.9 (3.5 TO 7.0) STERILE, NONPYROGENIC.

ADDITIVE MEDICATIONS SHOULD NOT BE DELIVERED VIA
PLASMA VOLUME EXPANDERS.

SINGLE-DOSE CONTAINER. CONTAINS NO BACTERIOSTAT.
DISCARD UNUSED PORTION. FOR INTRAVENOUS USE. USUAL
DOSAGE: SEE INSERT. STORE AT 20 TO 25°C (68 TO 77°F). [SEE
USP CONTROLLED ROOM TEMPERATURE.] PROTECT FROM
FREEZING. DO NOT USE IF CRYSTALLIZATION HAS OCCURRED.
USE ONLY IF SOLUTION IS CLEAR AND CONTAINER IS
UNDAMAGED. MUST NOT BE USED IN SERIES CONNECTIONS.

Rx ONLY

3
v
CONTAINS DEHP

Hospira

DISTRIBUTED BY HOSPIRA, INC.,
LAKE FOREST, IL 60045 USA

14478701
IM-4485

PRINCIPAL DISPLAY PANEL - 500 mL Bag Overwrap - 7419

2
HDPE

TO OPEN TEAR AT NOTCH

DO NOT REMOVE FROM OVERWRAP UNTIL READY FOR USE. AFTER REMOVING
THE OVERWRAP, CHECK FOR MINUTE LEAKS BY SQUEEZING CONTAINER
FIRMLY. IF LEAKS ARE FOUND, DISCARD SOLUTION AS STERILITY MAY BE
IMPAIRED. RECOMMENDED STORAGE: ROOM TEMPERATURE (25°C). AVOID
EXCESSIVE HEAT. PROTECT FROM FREEZING. SEE INSERT.
IM-4498

Not Made With Natural Rubber Latex

14622100